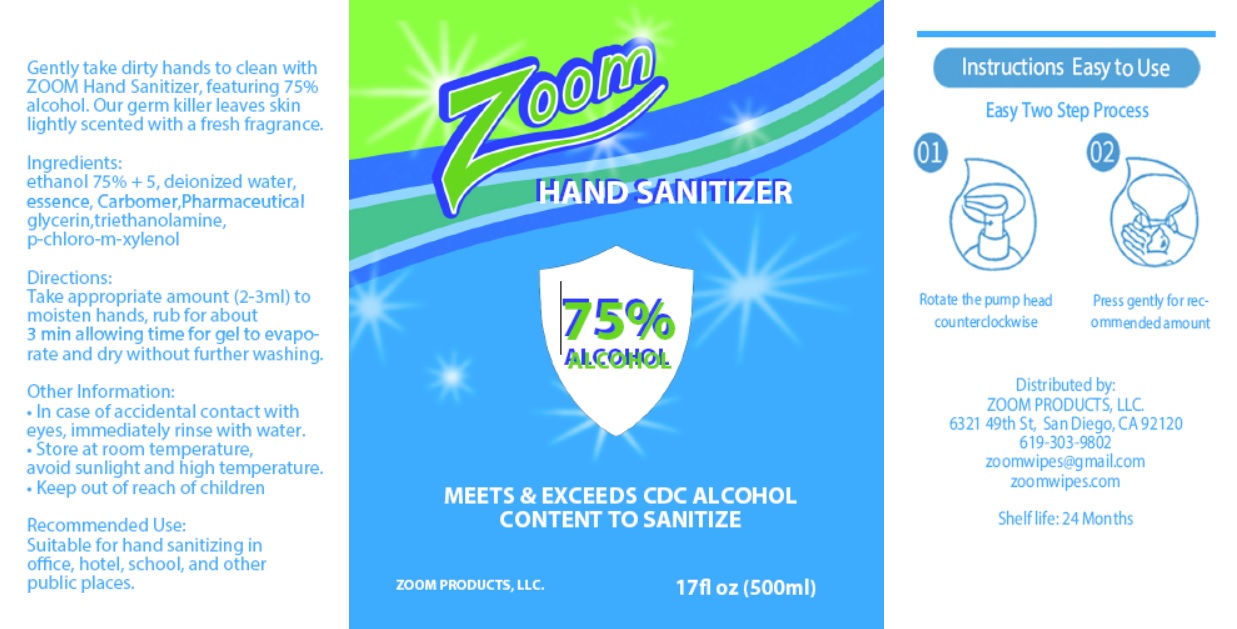 DRUG LABEL: ZOOM HAND SANITIZER
NDC: 70401-970 | Form: GEL
Manufacturer: Zoom Products, Llc.
Category: otc | Type: HUMAN OTC DRUG LABEL
Date: 20200429

ACTIVE INGREDIENTS: ALCOHOL 75 mL/100 mL
INACTIVE INGREDIENTS: WATER; CARBOMER HOMOPOLYMER, UNSPECIFIED TYPE; GLYCERIN; TROLAMINE; CHLOROXYLENOL

Zoom HAND SANITIZER

Ingredients:

ethanol 75%

PURPOSE

Antiseptic

INACTIVE INGREDIENT

deionized water, essence, Carbomer, Pharmaceutical glycerin, triethanolamine, p-chloro-m-xylenol

Directions:

Take appropriate amount (2-3ml) to moisten hands, rub for about 3 min allowing time for gel to evaporate and dry without further washing.

Other Information:

• In case of accidental contact with eyes, immediately rinse with water.
• Store at room temperature, avoid sunlight and high temperature.

• Keep out of reach of children

Recommended Use:

Suitable for hand sanitizing in office, hotel, school, and other public places.

Instructions Easy to Use

Easy Two Step Process

01 Rotate the pump head counterclockwise

02 Press gently for recommended amount

Gently take dirty hands to clean with ZOOM Hand Sanitizer, featuring 75% alcohol. Our germ killer leaves skin lightly scented with a fresh fragrance

MEETS & EXCEEDS CDC ALCOHOL CONTENT TO SANITIZE

Distributed by:
ZOOM PRODUCTS, LLC.
6321 49th St, San Diego, CA 92120
619-303-9802
zoomwipes@gmail.com
zoomwipes.com

Shelf life: 24 Month